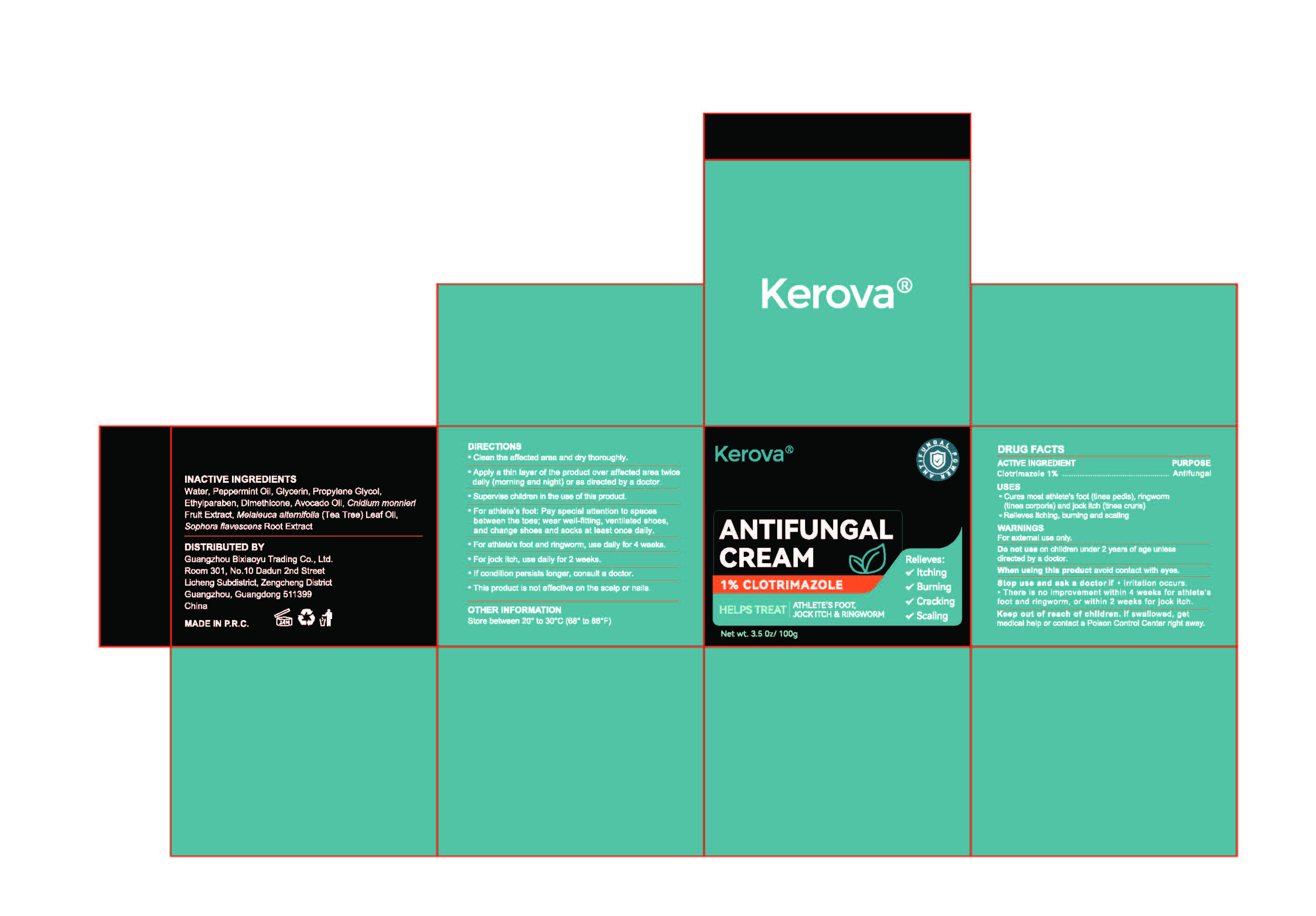 DRUG LABEL: Kerova  ANTIFUNGAL
NDC: 85959-002 | Form: CREAM
Manufacturer: Guangzhou Bixiaoyu Trading Co., Ltd.
Category: otc | Type: HUMAN OTC DRUG LABEL
Date: 20260210

ACTIVE INGREDIENTS: CLOTRIMAZOLE 1 g/100 g
INACTIVE INGREDIENTS: AVOCADO OIL; WATER; ETHYLPARABEN; PEPPERMINT OIL; SOPHORA FLAVESCENS ROOT; MELALEUCA ALTERNIFOLIA (TEA TREE) LEAF OIL; GLYCERIN; DIMETHICONE; PROPYLENE GLYCOL; CNIDIUM MONNIERI FRUIT

85959-002-01Kerova ANTIFUNGAL CREAM

ACTIVE INGREDIENT
Clotrimazole 1%
PURPOSEAntifungal

Keep out of reach of children. If swallowed, getmedical help or contact a Poison Control Center right away.

PURPOSE

Cures most athlete's foot (tinea pedis), ringworm(tinea corporis) and jock itch (tinea cruris)Relieves itching, burning and scaling

WARNINGS
For external use only.

DIRECTIONS
Clean the affected area and dry thoroughly.
·Apply a thin layer of the product over affected area twicedaily (morning and night) or as directed by a doctor.
Supervise children in the use of this product.
For athlete's foot: Pay special attention to spacesbetween the toes; wear well-fitting, ventilated shoes,and change shoes and socks at least once daily.

DOSAGE AND ADMINISTRATION

·For athlete's foot and ringworm, use daily for 4 weeks.
For jock itch, use daily for 2 weeks.
· If condition persists longer, consult a doctor.
This product is not effective on the scalp or nails

INACTIVE INGREDIENTS

Water, Peppermint Oil, Glycerin, Propylene Glycol,Ethylparaben, Dimethicone, Avocado Oil, Cnidium monnieriFruit Extract, Melaleuca alternifolia (Tea Tree) Leaf Oil,Sophora flavescens Root Extract